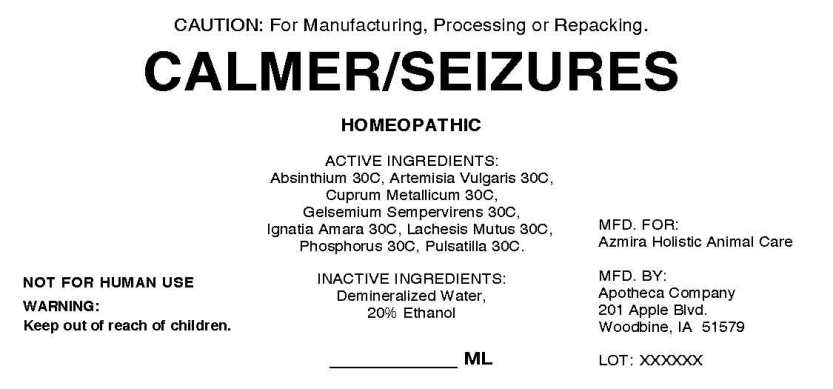 DRUG LABEL: Calmer/Seizures
NDC: 57520-0281 | Form: LIQUID
Manufacturer: Apotheca Company
Category: other | Type: BULK INGREDIENT
Date: 20211102

ACTIVE INGREDIENTS: WORMWOOD 30 [hp_C]/1 mL; ARTEMISIA VULGARIS ROOT 30 [hp_C]/1 mL; COPPER 30 [hp_C]/1 mL; GELSEMIUM SEMPERVIRENS ROOT 30 [hp_C]/1 mL; STRYCHNOS IGNATII SEED 30 [hp_C]/1 mL; LACHESIS MUTA VENOM 30 [hp_C]/1 mL; PHOSPHORUS 30 [hp_C]/1 mL; PULSATILLA VULGARIS 30 [hp_C]/1 mL
INACTIVE INGREDIENTS: WATER; ALCOHOL

Drug Facts

ACTIVE INGREDIENTS

Absinthium 30C, Artemisia vulgaris 30C, Cuprum metallicum 30C, Gelsemium sempervirens 30C, Ignatia amara 30C, Lachesis mutus 30C, Phosphorus 30C, Pulsatilla 30C.

PURPOSE

TO BE DETERMINED BY FINAL PROCESSOR

WARNINGS

NOT FOR HUMAN USE

WARNING:

Keep out of reach of children.

DOSAGE

TO BE DETERMINED BY FINAL PROCESSOR

INACTIVE INGREDIENTS

Demineralized water, 20% Ethanol.

KEEP OUT OF REACH OF CHILDREN

INDICATIONS

TO BE DETERMINED BY FINAL PROCESSOR

QUESTIONS

MFD. FOR:

Azmira Holistic Animal Care

MFD. BY:

Apotheca Company

201 Apple Blvd

Woodbine, IA 51579

PACKAGE LABEL DISPLAY

CAUTION: For Manufacturing, Processing or Repacking.

CALMER/SEIZURES

HOMEOPATHIC

4000 ML